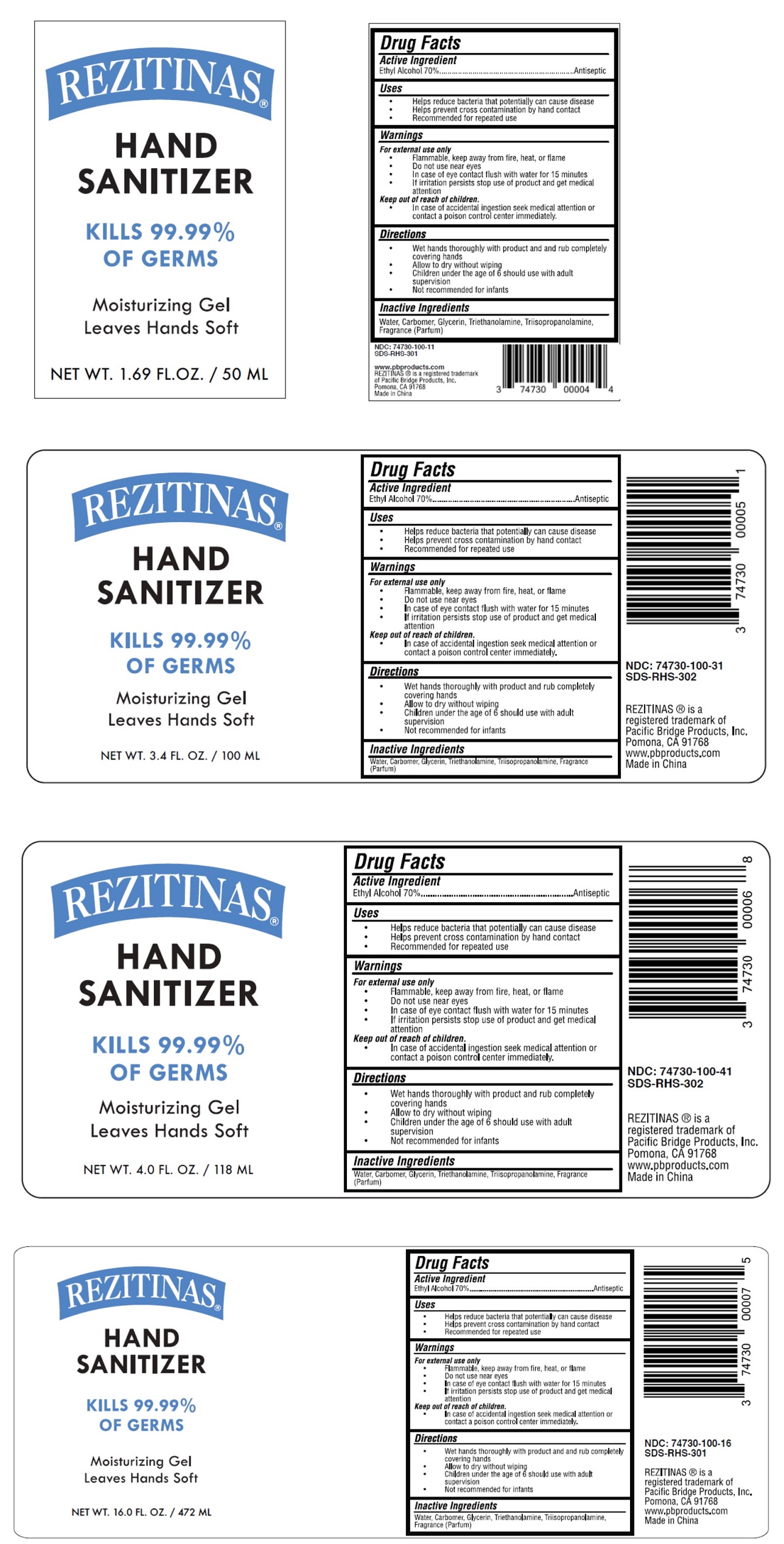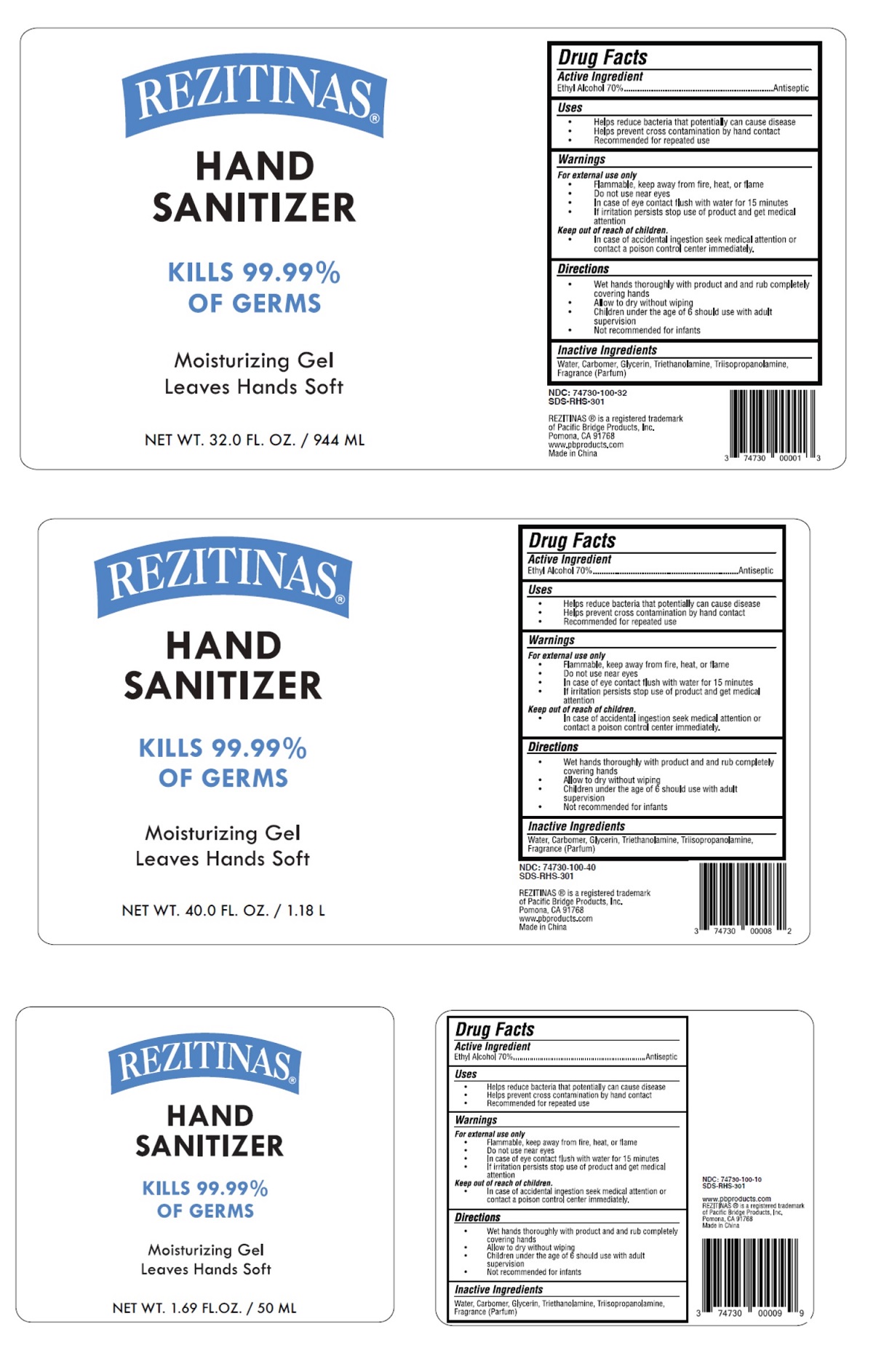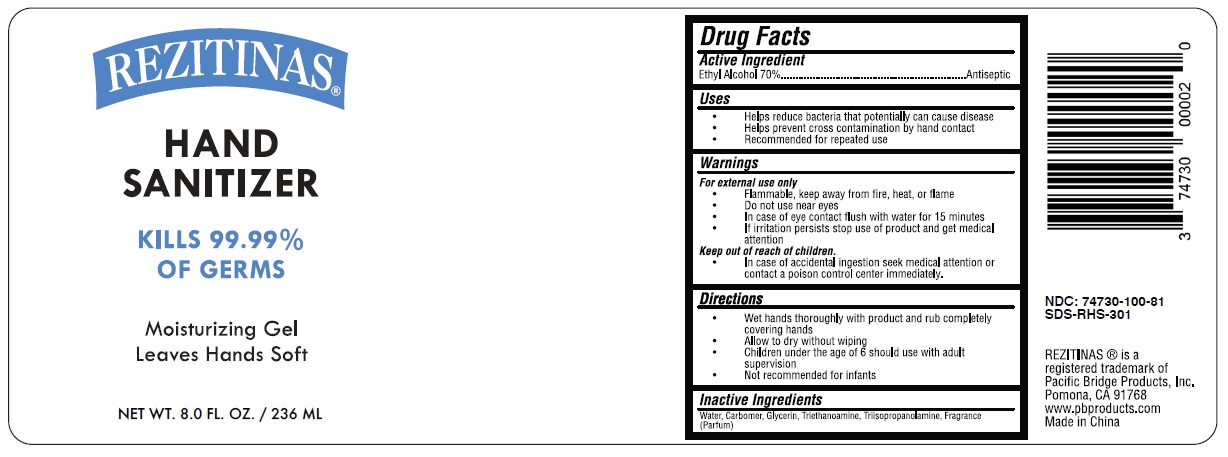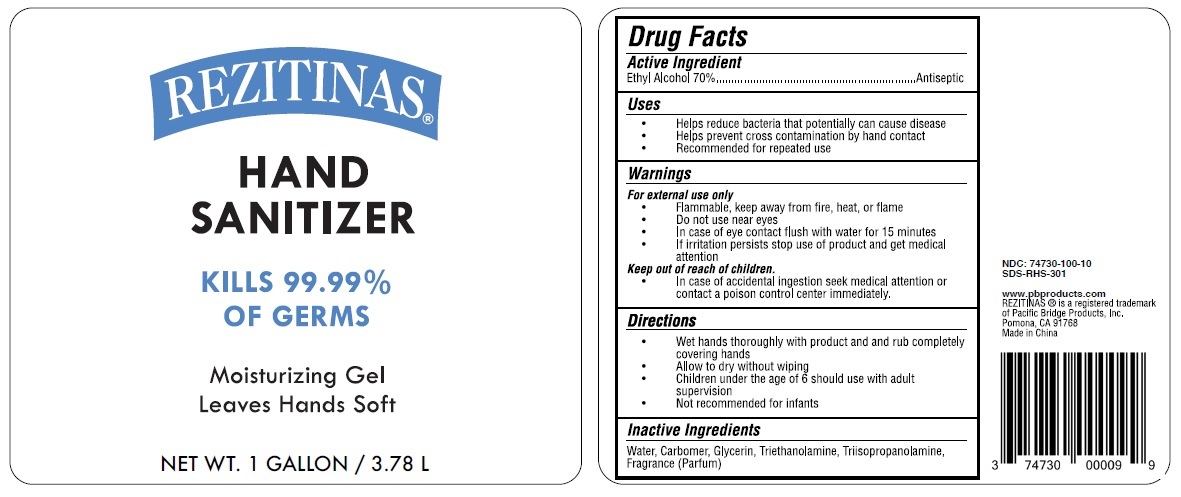 DRUG LABEL: REZITINAS HAND SANITIZER
NDC: 74730-100 | Form: GEL
Manufacturer: Pacific Bridge Products, Inc.
Category: otc | Type: HUMAN OTC DRUG LABEL
Date: 20200514

ACTIVE INGREDIENTS: ALCOHOL 70 mL/100 mL
INACTIVE INGREDIENTS: WATER; CARBOMER HOMOPOLYMER, UNSPECIFIED TYPE; GLYCERIN; TROLAMINE; TRIISOPROPANOLAMINE

REZITINAS® HAND SANITIZER

Active Ingredient

Ethyl Alcohol 70%

Purpose

Antiseptic

Uses

- Helps reduce bacteria that potentially can cause disease
- Helps prevent cross contamination by hand contact
- Recommended for repeated use

Warnings

For external use only

- Flammable, keep away from fire, heat, or flame
- Do not use near eyes
- In case of eye contact flush with water for 15 minutes
- If irritation persists stop use of product and get medical attention

Keep out of reach of children.

- In case of accidental ingestion seek medical attention or contact a poison control center immediately.

Directions

- Wet hands thoroughly with product and rub completely covering hands
- Allow to dry without wiping
- Children under the age of 6 should use with adult supervision
- Not recommended for infants

Inactive Ingredients

Water, Carbomer, Glycerin, Triethanolamine, Triisopropanolamine, Fragrance (Parfum)

KILLS 99.99% OF GERMS

Moisturizing Gel
Leaves Hands Soft

REZITINAS ® is a registered trademark of
Pacific Bridge Products, Inc.
Pomona, CA 91768
www.pbproducts.com
Made in China